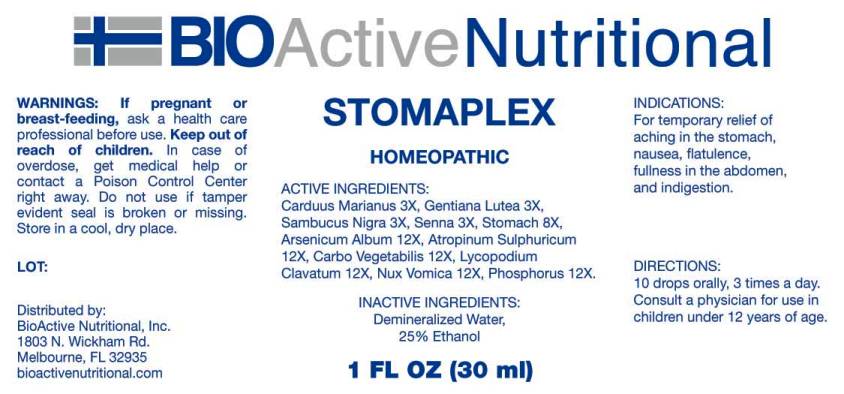 DRUG LABEL: Stomaplex
NDC: 43857-0644 | Form: LIQUID
Manufacturer: BioActive Nutritional, Inc.
Category: homeopathic | Type: HUMAN OTC DRUG LABEL
Date: 20240926

ACTIVE INGREDIENTS: MILK THISTLE 3 [hp_X]/1 mL; GENTIANA LUTEA ROOT 3 [hp_X]/1 mL; SAMBUCUS NIGRA FLOWERING TOP 3 [hp_X]/1 mL; SENNA LEAF 3 [hp_X]/1 mL; SUS SCROFA STOMACH 8 [hp_X]/1 mL; ARSENIC TRIOXIDE 12 [hp_X]/1 mL; ATROPINE SULFATE 12 [hp_X]/1 mL; ACTIVATED CHARCOAL 12 [hp_X]/1 mL; LYCOPODIUM CLAVATUM SPORE 12 [hp_X]/1 mL; STRYCHNOS NUX-VOMICA SEED 12 [hp_X]/1 mL; PHOSPHORUS 12 [hp_X]/1 mL
INACTIVE INGREDIENTS: WATER; ALCOHOL

DRUG FACTS:

ACTIVE INGREDIENTS:

Carduus Marianus 3X, Gentiana Lutea 3X, Sambucus Nigra 3X, Senna (Cassia Angustifolia) 3X, Stomach (Suis) 8X, Arsenicum Album 12X, Atropinum Sulphuricum 12X, Carbo Vegetabilis 12X, Lycopodium Clavatum 12X, Nux Vomica 12X, Phosphorus 12X.

PURPOSE:

For temporary relief of aching in the stomach, nausea, flatulence, fullness in the abdomen, and indigestion.

WARNINGS:

If pregnant or breast-feeding, ask a health care professional before use.

Keep out of reach of children. In case of overdose, get medical help or contact a Poison Control Center right away.

Do not use if tamper evident seal is broken or missing.

Store in cool, dry place.

DIRECTIONS:

10 drops orally, 3 times a day. Consult a physician for use in children under 12 years of age.

INACTIVE INGREDIENTS:

Demineralized Water, 25% Ethanol

INDICATIONS:

For temporary relief of aching in the stomach, nausea, flatulence, fullness in the abdomen, and indigestion.

QUESTIONS:

Distributed by:
BioActive Nutritional, Inc.
1803 N. Wickham Rd.
Melbourne, FL 32935
bioactivenutritional.com

PACKAGE LABEL DISPLAY:

BIOActiveNutritional

STOMAPLEX

HOMEOPATHIC

1 FL OZ (30 ml)